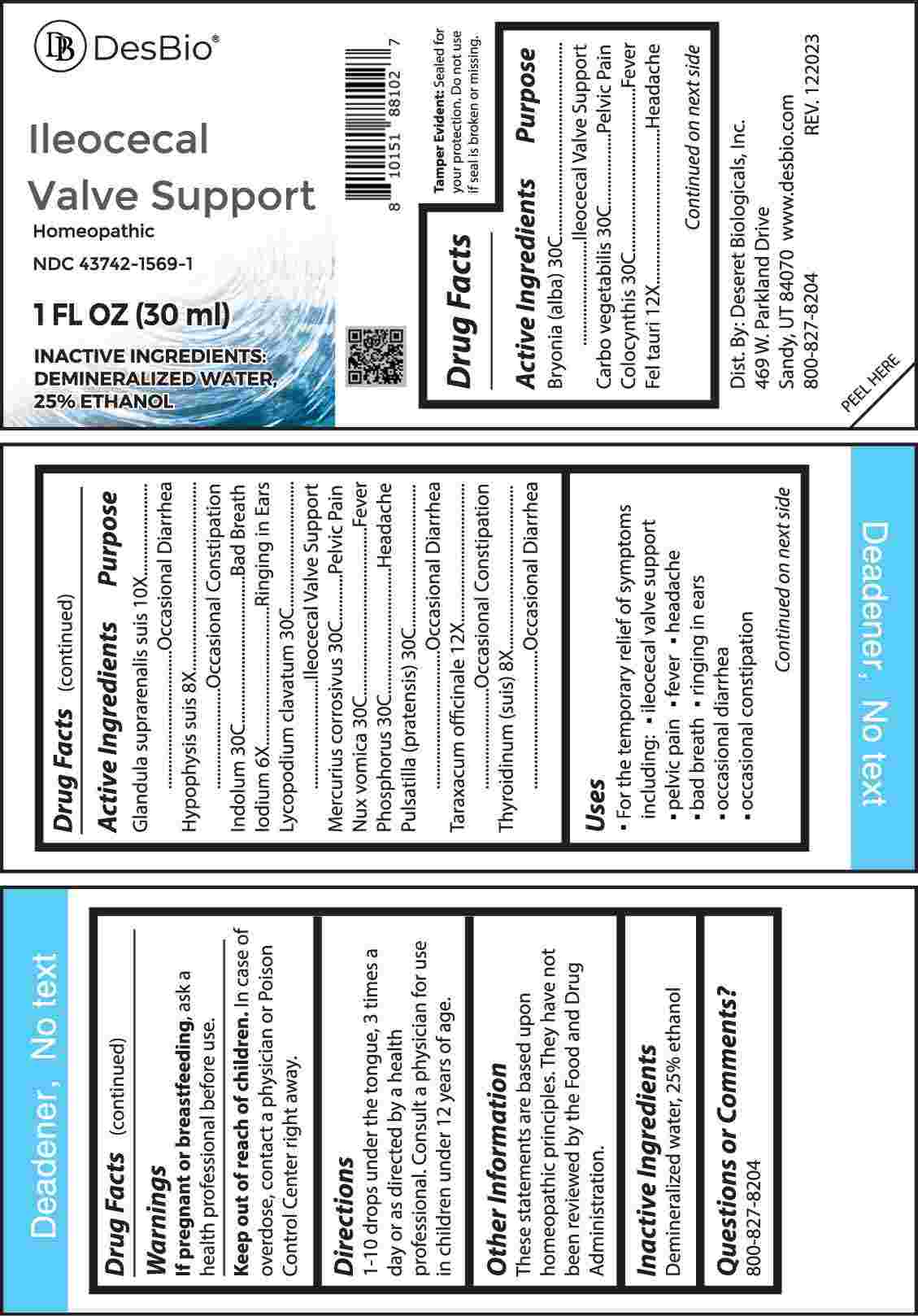 DRUG LABEL: Ileocecal Valve Support
NDC: 43742-1569 | Form: LIQUID
Manufacturer: Deseret Biologicals, Inc.
Category: homeopathic | Type: HUMAN OTC DRUG LABEL
Date: 20240415

ACTIVE INGREDIENTS: IODINE 6 [hp_X]/1 mL; SUS SCROFA PITUITARY GLAND 8 [hp_X]/1 mL; SUS SCROFA THYROID 8 [hp_X]/1 mL; SUS SCROFA ADRENAL GLAND 10 [hp_X]/1 mL; BOS TAURUS BILE 12 [hp_X]/1 mL; TARAXACUM OFFICINALE 12 [hp_X]/1 mL; BRYONIA ALBA ROOT 30 [hp_C]/1 mL; ACTIVATED CHARCOAL 30 [hp_C]/1 mL; CITRULLUS COLOCYNTHIS FRUIT PULP 30 [hp_C]/1 mL; INDOLE 30 [hp_C]/1 mL; LYCOPODIUM CLAVATUM SPORE 30 [hp_C]/1 mL; MERCURIC CHLORIDE 30 [hp_C]/1 mL; STRYCHNOS NUX-VOMICA SEED 30 [hp_C]/1 mL; PHOSPHORUS 30 [hp_C]/1 mL; PULSATILLA VULGARIS WHOLE 30 [hp_C]/1 mL
INACTIVE INGREDIENTS: WATER; ALCOHOL

DRUG FACTS:

ACTIVE INGREDIENT:

Bryonia (Alba) 30C, Carbo Vegetabilis 30C, Colocynthis 30C, Fel Tauri 12X, Glandula Suprarenalis Suis 10X, Hypophysis Suis 8X, Indolum 30C, Iodium 6X, Lycopodium Clavatum 30C, Mercurius Corrosivus 30C, Nux Vomica 30C, Phosphorus 30C, Pulsatilla (Pratensis) 30C, Taraxacum Officinale 12X, Thyroidinum (Suis) 8X.

PURPOSE:

Bryonia (Alba) – Ileocecal Valve Support, Carbo Vegetabilis – Pelvic Pain, Colocynthis - Fever, Fel Tauri - Headache, Glandula Suprarenalis Suis – Occasional Diarrhea, Hypophysis Suis – Occasional Constipation, Indolum – Bad Breath, Iodium – Ringing in Ears, Lycopodium Clavatum – Ileocecal Valve Support, Mercurius Corrosivus – Pelvic Pain, Nux Vomica - Fever, Phosphorus - Headache, Pulsatilla (Pratensis) – Occasional Diarrhea, Taraxacum Officinale – Occasional Constipation, Thyroidinum (Suis) – Occasional Diarrhea

USES:

• For the temporary relief of symptoms including:

• ileocecal valve support • pelvic pain • fever

• headache • bad breath • ringing in ears

• occasional diarrhea • occasional constipation

These statements are based upon homeopathic principles. They have not been reviewed by the Food and Drug Administration.

WARNINGS:

If pregnant or breast-feeding, ask a health professional before use.

Keep out of reach of children. In case of overdose, contact a physician or Poison Control Center right away.

Tamper Evident: Sealed for your protection. Do not use if seal is broken or missing.

KEEP OUT OF REACH OF CHILDREN:

In case of overdose, contact a physician or Poison Control Center right away.

DIRECTIONS:

1-10 drops under the tongue, 3 times a day or as directed by a health professional. Consult a physician for use in children under 12 years of age.

INACTIVE INGREDIENTS:

Demineralized water, 25% ethanol

QUESTIONS:

Dist. By: Deseret Biologicals, Inc.
469 W. Parkland Drive
Sandy, UT 84070

www.desbio.com

800-827-8204

PACKAGE LABEL DISPLAY:

Des Bio

Ileocecal Valve

Support

Homeopathic
NDC 43742-1569-1
1 FL OZ (30 ml)